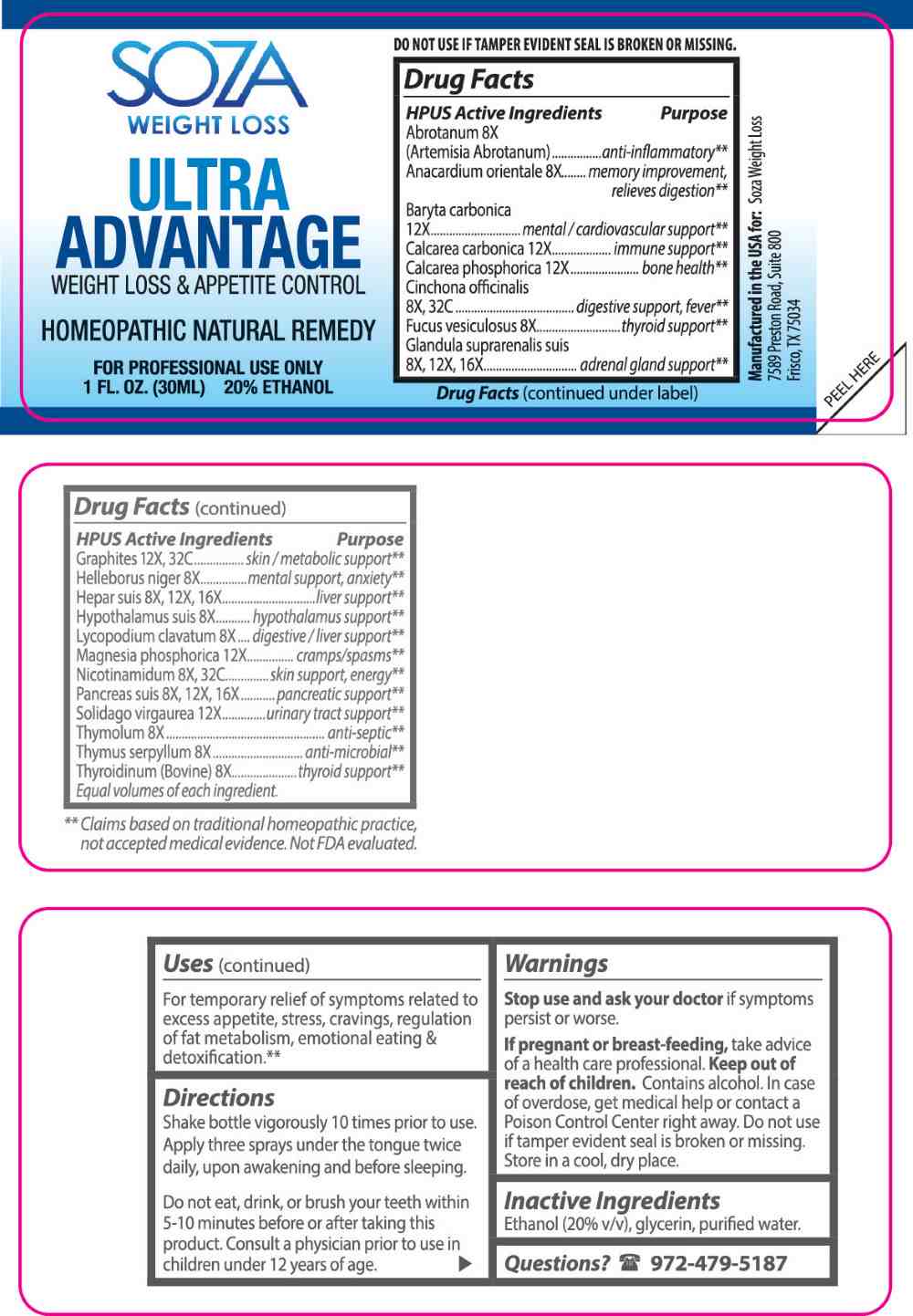 DRUG LABEL: Ultra Advantage
NDC: 69727-0003 | Form: LIQUID
Manufacturer: ELTTAC Inc DBA SWL
Category: homeopathic | Type: HUMAN OTC DRUG LABEL
Date: 20250603

ACTIVE INGREDIENTS: ARTEMISIA ABROTANUM FLOWERING TOP 8 [hp_X]/1 mL; SEMECARPUS ANACARDIUM JUICE 8 [hp_X]/1 mL; FUCUS VESICULOSUS 8 [hp_X]/1 mL; HELLEBORUS NIGER ROOT 8 [hp_X]/1 mL; SUS SCROFA HYPOTHALAMUS 8 [hp_X]/1 mL; LYCOPODIUM CLAVATUM SPORE 8 [hp_X]/1 mL; THYMOL 8 [hp_X]/1 mL; THYMUS SERPYLLUM WHOLE 8 [hp_X]/1 mL; THYROID, BOVINE 8 [hp_X]/1 mL; SUS SCROFA ADRENAL GLAND 8 [hp_X]/1 mL; PORK LIVER 8 [hp_X]/1 mL; SUS SCROFA PANCREAS 8 [hp_X]/1 mL; CINCHONA OFFICINALIS BARK 8 [hp_X]/1 mL; NIACINAMIDE 8 [hp_X]/1 mL; BARIUM CARBONATE 12 [hp_X]/1 mL; OYSTER SHELL CALCIUM CARBONATE, CRUDE 12 [hp_X]/1 mL; TRIBASIC CALCIUM PHOSPHATE 12 [hp_X]/1 mL; MAGNESIUM PHOSPHATE, DIBASIC TRIHYDRATE 12 [hp_X]/1 mL; SOLIDAGO VIRGAUREA FLOWERING TOP 12 [hp_X]/1 mL; GRAPHITE 12 [hp_X]/1 mL
INACTIVE INGREDIENTS: WATER; ALCOHOL; GLYCERIN

DRUG FACTS:

ACTIVE INGREDIENTS:

Abrotanum (Artemisia Abrotanum) 8X, Anacardium Orientale 8X, Baryta Carbonica 12X, Calcarea Carbonica 12X, Calcarea Phosphorica 12X, Cinchona Officinalis 8X, 32C, Fucus Vesiculosus 8X, Glandula Suprarenalis Suis 8X, 12X, 16X, Graphites 12X, 32C, Helleborus Niger 8X, Hepar Suis 8X, 12X, 16X, Hypothalamus Suis 8X, Lycopodium Clavatum 8X, Magnesia Phosphorica 12X, Nicotinamidum 8X, 32C, Pancreas Suis 8X, 12X, 16X, Solidago Virgaurea 12X, Thymolum 8X, Thymus Serpyllum 8X, Thyroidinum (Bovine) 8X.

PURPOSE:

Abrotanum (Artemisia Abrotanum) – anti-inflammatory,** Anacardium Orientale – memory improvement, relieves digestion,** Baryta Carbonica – mental/cardiovascular support,** Calcarea Carbonica – immune support,** Calcarea Phosphorica – bone health,** Cinchona Officinalis – digestive support, fever,** Fucus Vesiculosus – thyroid support,** Glandula Suprarenalis Suis – adrenal gland support,** Graphites – skin/metabolic support,** Helleborus Niger – mental support, anxiety,** Hepar Suis – liver support,** Hypothalamus Suis – hypothalamus support,** Lycopodium Clavatum – digestive/liver support,** Magnesia Phosphorica – cramps/spasms,** Nicotinamidum – skin support, energy**, Pancreas Suis – pancreatic support,** Solidago Virgaurea – urinary tract support,** Thymolum – anti-septic,** Thymus Serpyllum – anti-microbial,** Thyroidinum (Bovine) – thyroid support**
Equal volumes of each ingredient.
**Claims based on traditional homeopathic practice, not accepted medical evidence. Not FDA evaluated.

USES:

For temporary relief of symptoms related to excess appetite, stress, cravings, regulation of fat metabolism, emotional eating & detoxification.**

**Claims based on traditional homeopathic practice, not accepted medical evidence. Not FDA evaluated.

WARNINGS:

Stop use and ask your doctor if symptoms persist or worsen.

If pregnant or breast-feeding, take advice of a healthcare professional.

Keep out of reach of children. Contains alcohol. In case of overdose, get medical help or contact a Poison Control Center right away.

Do not use if tamper evident seal is broken or missing.

Store in a cool dry place.

KEEP OUT OF REACH OF CHILDREN:

Contains alcohol. In case of overdose, get medical help or contact a Poison Control Center right away.

DIRECTIONS:

Shake bottle vigorously 10 times prior to use. Apply three sprays under the tongue twice daily, upon awakening and before sleeping. Do not eat, drink, or brush your teeth within 5-10 minutes before or after taking this product. Consult a physician prior to use in children under 12 years of age.

INACTIVE INGREDIENTS:

Ethanol (20% v/v), glycerin, purified water.

QUESTIONS:

Manufactured in the USA for:

Soza Weight Loss

7589 Preston Road, Suite 800

Frisco, TX, 75034

972-479-5187

PACKAGE LABEL DISPLAY:

SOZA

WEIGHT LOSS

ULTRA ADVANTAGE

WEIGHT LOSS & APPETITE CONTROL

HOMEOPATHIC NATURAL REMEDY

FOR PROFESSIONAL USE ONLY

1 FL OZ (30ML)